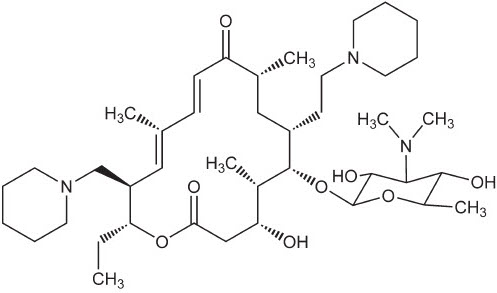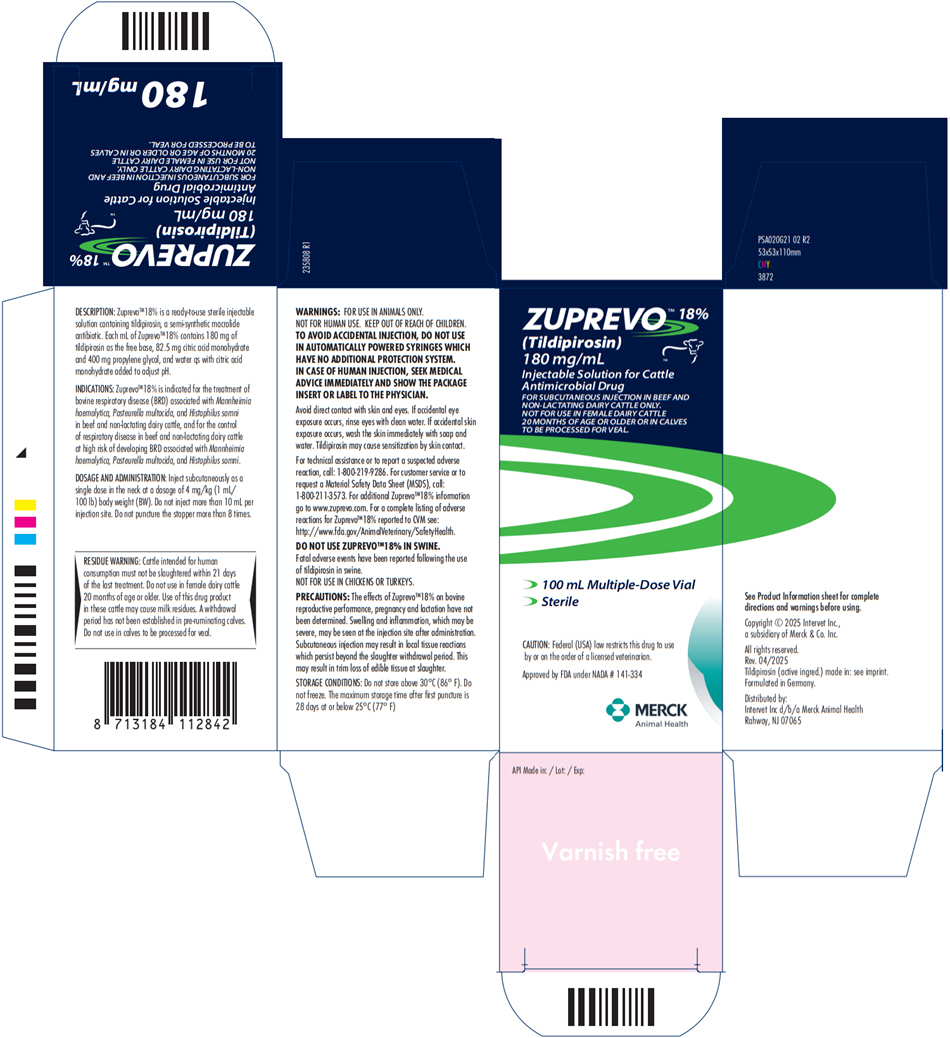 DRUG LABEL: Zuprevo
NDC: 0061-4321 | Form: INJECTION, SOLUTION
Manufacturer: Merck Sharp & Dohme Corp.
Category: animal | Type: PRESCRIPTION ANIMAL DRUG LABEL
Date: 20250915

ACTIVE INGREDIENTS: TILDIPIROSIN 180 mg/1 mL

ZUPREVO™ 18%
(Tildipirosin)
Injectable Solution for Cattle

235802 R2

Antimicrobial Drug

180 mg of tildipirosin/mL

For subcutaneous injection in beef and non-lactating dairy cattle only.

Not for use in female dairy cattle 20 months of age or older or in calves to be processed for veal.

CAUTION:

Federal (USA) law restricts this drug to use by or on the order of a licensed veterinarian.

DESCRIPTION:

Zuprevo™18% is a ready-to-use sterile injectable solution containing tildipirosin, a semi-synthetic macrolide antibiotic. Each mL of Zuprevo™18% contains 180 mg of tildipirosin as the free base, 82.5 mg citric acid monohydrate and 400 mg propylene glycol, and water qs with citric acid monohydrate added to adjust pH.

CHEMICAL NOMENCLATURE AND STRUCTURE: Tildipirosin is the nonproprietary name for (11E,13E)-(4R,5S,6S,7R,9R,15R,16R)-6-(4-Dimethylamino-3,5-dihydroxy-6-methyl-tetrahydro-pyran-2-yloxy)-16-ethyl-4-hydroxy-5,9,13-trimethyl-7-(2-piperidin-1-yl-ethyl)-15-piperidin-1-ylmethyl-oxacyclohexadeca-11,13-diene-2,10-dione. The empirical formula is C41H71N3O8. The chemical structure of tildipirosin is shown below.

Figure 1

VETERINARY INDICATIONS

INDICATIONS: Zuprevo™18% is indicated for the treatment of bovine respiratory disease (BRD) associated with Mannheimia haemolytica, Pasteurella multocida, and Histophilus somni in beef and and non-lactating dairy cattle, and for the control of respiratory disease in beef and non-lactating dairy cattle at high risk of developing BRD associated with Mannheimia haemolytica, Pasteurella multocida, and Histophilus somni.

DOSAGE AND ADMINISTRATION: Inject subcutaneously as a single dose in the neck at a dosage of 4 mg/kg (1 mL/100 lb) body weight (BW). Do not inject more than 10 mL per injection site. Do not puncture the stopper of the respective vial size more than the tested number of punctures, shown in Table 1.

Clinical field studies indicate that administration of Zuprevo™ 18% (tildipirosin) Injectable Solution is effective for the control of respiratory disease in beef and non-lactating dairy cattle at "high risk" of developing BRD. Calves at high risk of developing BRD typically experience one or more of the following risk factors:

- Commingling from multiple sale barns/sources
- Extended transport times and shrink
- Exposure to wet or cold weather conditions or wide temperature swings
- Stressful arrival processing procedures (such as castration, dehorning, or branding)
- Recent weaning and poor vaccination history

Table 1 Number of punctures tested in the in-use study for the respective vial sizes
Vial size [mL] | Number of punctures tested in the in-use study
100 | 8
250 | 16

WARNINGS

WARNINGS: FOR USE IN ANIMALS ONLY. NOT FOR HUMAN USE. KEEP OUT OF REACH OF CHILDREN. TO AVOID ACCIDENTAL INJECTION, DO NOT USE IN AUTOMATICALLY POWERED SYRINGES WHICH HAVE NO ADDITIONAL PROTECTION SYSTEM. IN CASE OF HUMAN INJECTION, SEEK MEDICAL ADVICE IMMEDIATELY AND SHOW THE PACKAGE INSERT OR LABEL TO THE PHYSICIAN.

Avoid direct contact with skin and eyes. If accidental eye exposure occurs, rinse eyes with clean water. If accidental skin exposure occurs, wash the skin immediately with soap and water. Tildipirosin may cause sensitization by skin contact.

For technical assistance or to report a suspected adverse reaction, call: 1-800-219-9286.

For customer service or to request a Material Safety Data Sheet (MSDS), call: 1-800-211-3573.

For additional Zuprevo™18% information go to www.zuprevo.com.

For a complete listing of adverse reactions for Zuprevo™18% reported to CVM see: http://www.fda.gov/AnimalVeterinary/SafetyHealth.

DO NOT USE ZUPREVO 18% IN SWINE. Fatal adverse events have been reported following the use of tildipirosin in swine. NOT FOR USE IN CHICKENS OR TURKEYS.

RESIDUE WARNING

RESIDUE WARNING: Cattle intended for human consumption must not be slaughtered within 21 days of the last treatment. Do not use in female dairy cattle 20 months of age or older. Use of this drug product in these cattle may cause milk residues. A withdrawal period has not been established in pre-ruminating calves. Do not use in calves to be processed for veal.

PRECAUTIONS

PRECAUTIONS: The effects of Zuprevo™18% on bovine reproductive performance, pregnancy and lactation have not been determined. Swelling and inflammation, which may be severe, may be seen at the injection site after administration. Subcutaneous injection may result in local tissue reactions which persist beyond the slaughter withdrawal period. This may result in trim loss of edible tissue at slaughter.

CLINICAL PHARMACOLOGY

CLINICAL PHARMACOLOGY: Similar to other macrolides, tildipirosin inhibits essential bacterial protein biosynthesis with selective binding to ribosomal subunits in a bacteriostatic and time-dependent manner. Tildipirosin may be bactericidal against certain isolates of Mannheimia haemolytica and Pasteurella multocida.

The following plasma pharmacokinetic (PK) properties of tildipirosin have been observed following a subcutaneous injection at a dose of 4 mg/kg body weight in the neck:

Table 2 Summary of pharmacokinetic characterization of tildipirosin administered subcutaneously to calves at a dose of 4 mg/kg BW.
Parameter | Average | SD
Cmax (ng/mL) | 767 [Value based on all 14 animals] | 284
Tmax (hr) | 0.75 | 0.43
AUC0-last (hr∙ng/mL) | 21017 [Value based on 8 animals that were slaughtered at 504 hr post-treatment.] | 3499
AUC0-inf (hr∙ng/mL) | 24934 | 3508
t1/2 (hr) | 210 | 53
Cmax: maximum observed plasma concentration
Tmax: Time at which Cmax was observed
AUC0-last: Area under the plasma concentration versus time curve measured from time zero to the last sample with tildipirosin concentrations exceeding the limit of quantification of the analytical method
AUC0-inf: AUC estimated from time zero to time infinity
t1/2: Terminal elimination half life

Due to the extensive partitioning of macrolides into tissues and because of their multi-fold greater concentrations in bronchial fluid relative to that observed in the blood, plasma drug concentrations underestimate concentrations at the site of action [Nightingale, C.H. (1997) Pharmacokinetics and pharmacodynamics of newer macrolides. The Pediatric Infectious Disease Journal, 16, 438-443.] . This is shown for tildipirosin in the following table, where bronchial fluid samples were collected in live, healthy calves, and compared to the concentrations in plasma observed in these same animals:

Table 3 Bronchial fluid-to-plasma ratio of tildipirosin in non-anesthetized cattle following a subcutaneous injection at a dose of 4 mg/kg body weight in the neck
Time (hours) | Bronchial fluid (BF) concentration (ng/g) |  | Plasma (P) concentration (ng/mL) |  | BF/P Ratio
 | Average | SD | Average | SD
4 | 1543 | 895 | 297 | 81.8 | 5.20
10 | 2975 | 1279 | 242 | 96.7 | 12.3
24 | 3448 | 1433 | 136 | 53.9 | 25.4
72 | 3489 | 1712 | 70.7 | 29.0 | 49.3
96 | 1644 | 2024 | 60.2 | 29.0 | 27.3
120 | 1619 | 1629 | 52.3 | 19.9 | 30.9
240 | 1937 | 1416 | 27.1 | 10.8 | 71.5
336 | 1225 | 1682 | 26.1 | 9.2 | 47.0
504 | 935 | 1032 | 16.8 | 1.7 | 55.6

Tildipirosin concentrations in bronchial fluid collected in vivo from non-anesthetized cattle reflect the bacterial exposure to drug concentrations at the site of action.

MICROBIOLOGY

MICROBIOLOGY: Tildipirosin has shown in vitro and in vivo antibacterial activity against the bacteria Mannheimia haemolytica, Pasteurella multocida, and Histophilus somni, three pathogens associated with bovine respiratory disease (BRD).

The minimum inhibitory concentrations (MICs) of tildipirosin against the indicated BRD pathogens were determined using the methods described in the M31-A2 standard of the Clinical and Laboratory Standards Institute (CLSI) and are shown in Table 4.

The MICs of tildipirosin were determined for isolates of Mannheimia haemolytica, Pasteurella multocida, and Histophilus somni obtained from two BRD field studies. In both studies, tested isolates of M. haemolytica and P. multocida were obtained from nasopharyngeal swabs taken prior to treatment from all study animals. Tested isolates of H. somni were obtained from nasopharyngeal swabs taken prior to treatment from all study animals and from nasopharyngeal swabs taken from saline-treated animals classified as treatment failures.

Table 4 Tildipirosin minimum inhibitory concentration (MIC) values [The correlation between in vitro susceptibility data and clinical effectiveness is unknown.] of indicated pathogens isolated from BRD field studies in the U.S.
Indicated Pathogens | Year of isolation | Study | Number of isolates | MIC50 [The lowest MIC to encompass 50% and 90% of the most susceptible isolates, respectively.] (μg/mL) | MIC90 (μg/mL) | MIC range (μg/mL)
Mannheimia haemolytica | 2007 | Treatment | 484 | 1 | 2 | 0.25 to >32
Mannheimia haemolytica | 2007 to 2008 | Control | 178 | 1 | 1 | 0.25 to >32
Pasteurella multocida | 2007 | Treatment | 235 | 0.5 | 1 | 0.12 to >32
Pasteurella multocida | 2007 to 2008 | Control | 273 | 0.5 | 1 | ≤0.03 to 4
Histophilus somni | 2007 | Treatment | 33 | 2 | 4 | 1 to 4
Histophilus somni | 2007 to 2008 | Control | 32 | 2 | 4 | 1 to >32

EFFECTIVENESS: In a multi-location field study, calves with naturally occurring BRD were treated with tildipirosin. The treatment success rate of the tildipirosin-treated group was compared to the treatment success rate in the saline-treated control group. A treatment success was defined as a calf not designated as a treatment failure from Day 1 to 13 and with normal attitude, normal respiration, and a rectal temperature of < 104°F on Day 14. The treatment success rate was significantly higher (p = 0.003) for the tildipirosin-treated group (229/300, 76%) compared to the saline-treated control group (96/200, 32%). There were no BRD-related deaths in the tildipirosin-treated group compared to a 7% (21/300) BRD-related mortality rate in the saline-treated group.

In another multi-location field study, calves at high risk for developing BRD were administered tildipirosin. The treatment success rate of the tildipirosin-treated group was compared to the treatment success rate in the saline-treated control group. A treatment success was defined as a calf not designated as a treatment failure based on clinical respiratory and attitude scoring and, if necessary, rectal temperature measurement of < 104°F through the end of the study (Day 14). The treatment success rate was significantly higher (p = 0.0001) for the tildipirosin-treated group (305/386, 79%) compared to the saline-treated group (197/387, 51%). There were three BRD-related deaths during the study (one tildipirosin-treated calf and two saline treated calves).

ANIMAL SAFETY: A target animal safety study was conducted using Zuprevo™18% administered in 5-month-old cattle as three subcutaneous doses of 4, 12, or 20 mg/kg BW given 7 days apart (1×, 3×, and 5× the labeled dose). Animals remained clinically healthy during the study at the labeled dose. Injection site swelling and inflammation, initially severe in some animals, was observed that persisted to the last day of observation (21 days after injection). No other drug-related lesions were observed macroscopically or microscopically at the labeled dose.

A separate injection site tolerance study was conducted using Zuprevo™18% in 5- to 9-month-old cattle administered as a single subcutaneous injection of 10 mL. Injection site swelling and inflammation, initially severe in some animals, was observed that persisted to the last day of observation (35 days after injection). No other drug-related clinical signs were observed.

STORAGE AND HANDLING

STORAGE CONDITIONS: Do not store above 30°C (86°F). Do not freeze. The maximum storage time after first puncture is 28 days at or below 25°C (77°F).

HOW SUPPLIED

HOW SUPPLIED: Zuprevo™18% is supplied in 100 and 250 mL, amber glass, sterile, multi-dose vials.

U. S. Patent: 6,514,946

Approved by FDA under NADA # 141-334
Use Only as Directed
Copyright © 2025 Intervet Inc., a subsidiary of Merck & Co.
All rights reserved.
Rev. 04/2025
Formulated in Germany.
Distributed by: Intervet Inc d/b/a Merck Animal Health, Rahway, NJ 07065

PRINCIPAL DISPLAY PANEL - 100 mL Vial Carton

ZUPREVO™ 18%
(Tildipirosin)
180 mg/mL

Injectable Solution for Cattle
Antimicrobial Drug

FOR SUBCUTANEOUS INJECTION IN BEEF AND
NON-LACTATING DAIRY CATTLE ONLY.
NOT FOR USE IN FEMALE DAIRY CATTLE
20 MONTHS OF AGE OR OLDER OR IN CALVES
TO BE PROCESSED FOR VEAL.

100 mL Multiple-Dose Vial
Sterile

CAUTION: Federal (USA) law restricts this drug to use
by or on the order of a licensed veterinarian.

Approved by FDA under NADA # 141-334

MERCK
Animal Health